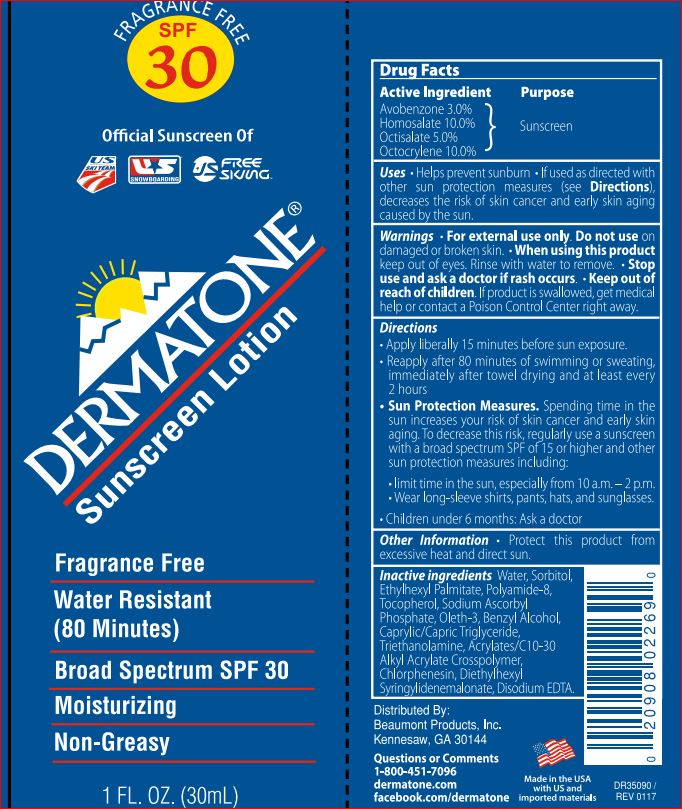 DRUG LABEL: Dermatone Sunscreen SPF 30
NDC: 65449-001 | Form: LOTION
Manufacturer: Beaumont Products
Category: otc | Type: HUMAN OTC DRUG LABEL
Date: 20180608

ACTIVE INGREDIENTS: Avobenzone 3 g/100 mL; Homosalate 10 g/100 mL; Octisalate 5 g/100 mL; Octocrylene 10 g/100 mL
INACTIVE INGREDIENTS: CARBOMER INTERPOLYMER TYPE A (ALLYL SUCROSE CROSSLINKED); Benzyl Alcohol; MEDIUM-CHAIN TRIGLYCERIDES; Chlorphenesin; Diethylhexyl Syringylidenemalonate; EDETATE DISODIUM; Ethylhexyl Palmitate; Oleth-3; Sodium Ascorbyl Phosphate; Sorbitol; Tocopherol; TROLAMINE; Water

Drug Facts

Active ingredient

Avobenzone - 3.00%
Homosalate - 10.00%
Octisalate - 5.00%
Octocrylene - 10.00%

Purpose

Sunscreen

Uses

Uses • helps prevent sunburn • if used as directed with other sun protection mesures (see Direction) decreases the risk of skin cancer

WarningFor external use only

do not use on damaged or broken skin

When using this product keep out of eyes. Rinse with water to remove.

Stop use and ask a doctor if rash occurs.

Keep out of reach of children.

If product is swallowed, get medical help or contact a Poison Control Center right away.

Directions

apply liberally 15 minutes before sun exposure
reapply:
after 80 minutes of swimming or sweating
immediately after towel drying
at least 2 hours
Sun Protection Measures. Spending time in the sun increases your risk of skin cancer and early skin aging. To decrease this risk, regularly use a sunscreen with a broad spectrum SPF of 15 or higher and other sun protection measures including:
limit time in the sun, especially from 10 a.m. -2 p.m.
wear long-sleeve shirts, pants, hats, and sunglasses
children under 6 months: Ask a doctor

Other Information

protect this product from excessive heat and direct sun

Inactive Ingredients:
Acrylates/C10-30 Alkyl Acrylate Crosspolymer
Benzyl Alcohol
Caprylic/Capric Triglyceride
Chlorphenesin
Diethylhexyl Syringylidenemalonate
Disodium EDTA
Ethylhexyl Palmitate
Oleth-3
Polyamide-8
Sodium Ascorbyl Phosphate
Sorbitol
Tocopherol
Triethanolamine
Water